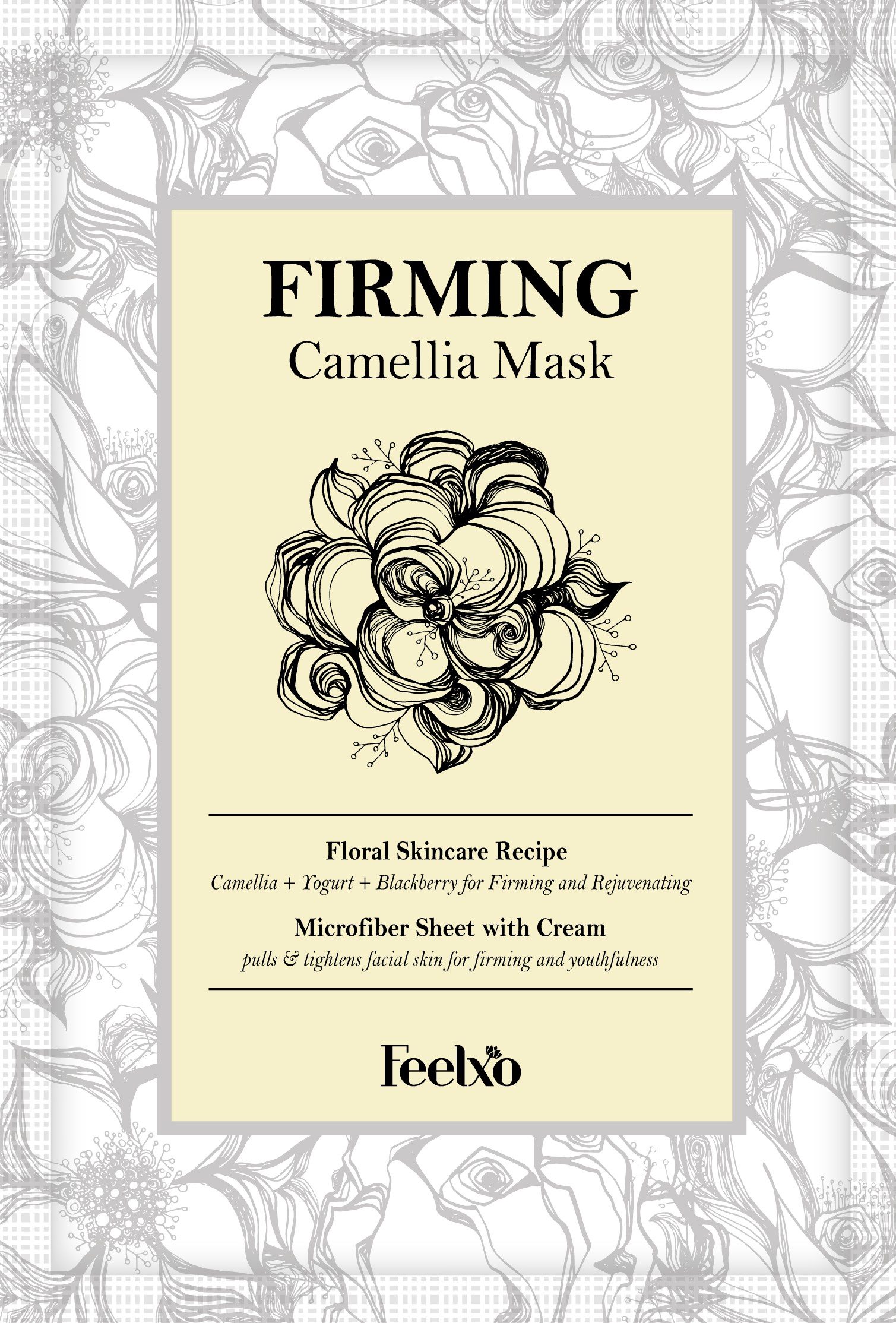 DRUG LABEL: FIRMING Camellia Mask
NDC: 71694-0003 | Form: LIQUID
Manufacturer: Feelxo
Category: otc | Type: HUMAN OTC DRUG LABEL
Date: 20181114

ACTIVE INGREDIENTS: GLYCERIN 5 g/100 mL
INACTIVE INGREDIENTS: WATER; BUTYLENE GLYCOL

Drug Facts

ACTIVE INGREDIENT

Glycerin

INACTIVE INGREDIENT

Water, Butylene Glycol, etc.

PURPOSE

Skin Protectant

keep out of reach of the children

INDICATIONS AND USAGE

1. 1. Cleanse and tone the skin.
2. Unfold the mask and carefully adjust it onto your face.
3. Leave the mask on your face for 15~20 minutes for best outcome.
4. Remove the mask and gently massage excess serum for better absorption.

WARNINGS

- Keep the mask in the fridge before use to enjoy more cooling & soothing effect
- Feelxo sheet mask can be used for all skin types, however it is not recommended for those who need medical skin care.

DOSAGE AND ADMINISTRATION

for external use only